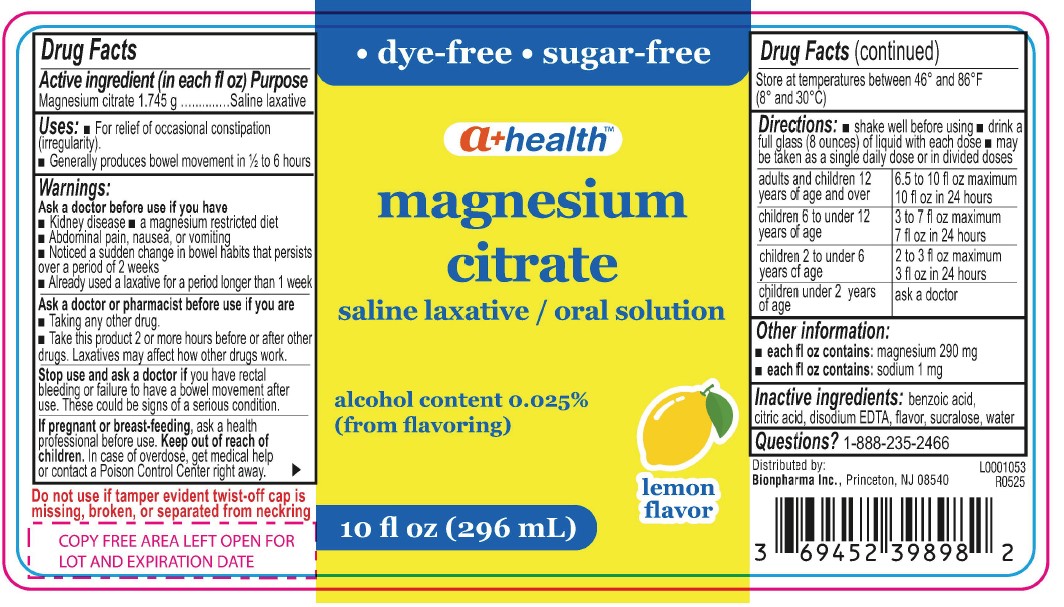 DRUG LABEL: Magnesium Citrate
NDC: 69452-398 | Form: LIQUID
Manufacturer: Bionpharma, Inc.
Category: otc | Type: HUMAN OTC DRUG LABEL
Date: 20250930

ACTIVE INGREDIENTS: MAGNESIUM CITRATE 1.745 g/29.6 mL
INACTIVE INGREDIENTS: BENZOIC ACID; WATER; CITRIC ACID MONOHYDRATE; SUCRALOSE; EDETATE DISODIUM ANHYDROUS

A+ Health Magnesium Citrate Oral Solution - Lemon

Active Ingredient

Magnesium citrate 1.745g per fl oz

Purpose

Saline Laxtive

Uses

■ For relief of occasional constipation (irregularity).
■ Generally produces bowel movement in ½ to 6 hours

Warnings

Ask a doctor before use if you have
■ Kidney disease ■ a magnesium restricted diet
■ Abdominal pain, nausea, or vomiting
■ Noticed a sudden change in bowel habits that persists over a period of 2 weeks
■ Already used a laxative for a period longer than 1 week

Ask a doctor or pharmacist before use if you are

■ Taking any other drug.
■ Take this product 2 or more hours before or after other drugs. Laxatives may affect how other drugs work.

Stop use and ask a doctor if

you have rectal bleeding or failure to have a bowel movement after use. These could be signs of a serious condition.

If pregnant or breast-feeding,

ask health professional before use.

Keep out of reach of children.

In case of overdose, get medical help or contact a Poison Control Center right away.

Other Information

Store at temperatures between 46° and 86°F (8° and 30° C)

Directions

shake well before using ■ drink a full glass (8 ounces) of liquid with each dose ■ may be taken as a single daily dose or in divided doses

adults and children 12 years of age and over | 6.5 to 10 fl oz maximum; 10 fl oz in 24 hours
children 6 to under 12 years of age | 3 to 7 fl oz maximum; 7 fl oz in 24 hours
children 2 to under 6 years of age | 2 to 3 fl oz maximum 3 fl oz in 24 hours
children under 2 years of age | ask a doctor

Other Information

■ each fl oz contains: magnesium 290 mg
■ each fl oz contains: sodium 1 mg

Inactive Ingredients

benzoic acid, citric acid, disodium EDTA, flavor, sucralose, water

Questions?

1-888-235-2466

Do not use if tamper evident twist-off cap is missing, broken, or separated from neckring
Distributed by:
Bionpharma Inc., Princeton, NJ 08540

L0001053

R0525

10 fl oz bottle label

• dye-free • sugar-free

a+ healthTM

magnesium
citrate
saline laxative / oral solution
alcohol content 0.025%
(from flavoring)
lemon
flavor
10 fl oz (296 mL)